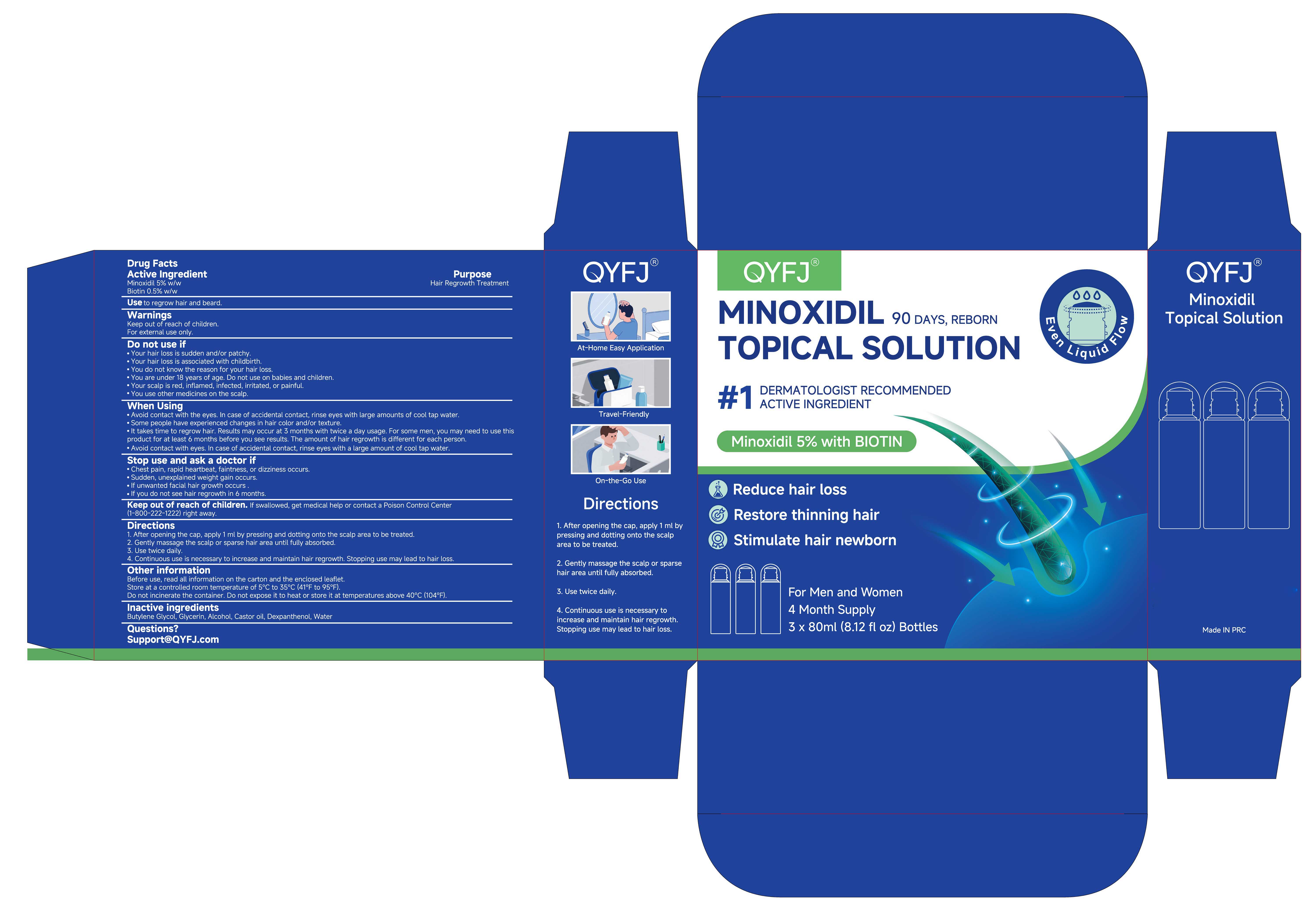 DRUG LABEL: 5% Minoxidil Hair Growth Topical Solution
NDC: 87112-001 | Form: LIQUID
Manufacturer: Yiwu Pu Feather Trading Co., LTD
Category: otc | Type: HUMAN OTC DRUG LABEL
Date: 20251231

ACTIVE INGREDIENTS: MINOXIDIL 5 g/100 mL; BIOTIN 0.5 g/100 mL
INACTIVE INGREDIENTS: WATER; CASTOR OIL; DEXPANTHENOL; GLYCERIN; ALCOHOL; BUTYLENE GLYCOL

87112-001 5% Minoxidil Hair Growth Topical Solution

ACTIVE INGREDIENT

Minoxidil 5%
Biotin 0.5%

PURPOSE

Hair Regrowth Treatment

INDICATIONS AND USAGE

Use to regrow hair and beard.

Keep out of reach of children.

For external use only

DO NOT USE

Your hair loss is sudden and/or patchy.
Your hair loss is associated with childbirth.
You do not know the reason for your hair loss.
You are under 18 years of age. Do not use on babies and children.
Your scalp is red, inflamed, infected, irritated, or painful.
You use other medicines on the scalp.

WHEN USING

Avold contact with the eves. in case of accidental contact, rinse eves with large amounts of cool tap water
Some people have experienced changes in hair color and/or texture.
It takes time to regrow hair. Results may occur at 3 months with twice a day usage. For some men, you may need to use this product for at least 6 months before you see results. The amount of hair regrowth is diferent for each person.
Avoid contact with eyes. in case of accidental contact, rinse eyes with a large amount of cool tap water.

STOP USE

Chest pain, rapid heartbeat, faintness, or dizziness occurs.
Sudden, unexplained weight gain occurs.
lf unwanted facial hair growth occurs
lf you do not see hair regrowth in 6 months.

Keep out of reach of children. f swallowed, get medical help or contact a Poison Control Center
(1-800-222-1222)right away.

DOSAGE AND ADMINISTRATION

1. After opening the cap, apply 1 ml by pressing and dotting onto the scalp area to be treated.
2. Gently massage the scalp or sparse hair area until fully absorbed.
3. Use twice daily.
4. Continuous use is necessary to increase and maintain har regrowth. Stopping use may lead to hair loss

INACTIVE INGREDIENT

Butylene Glycol
Glycerin
Alcohol
Castor oil
Dexpanthenol
Water